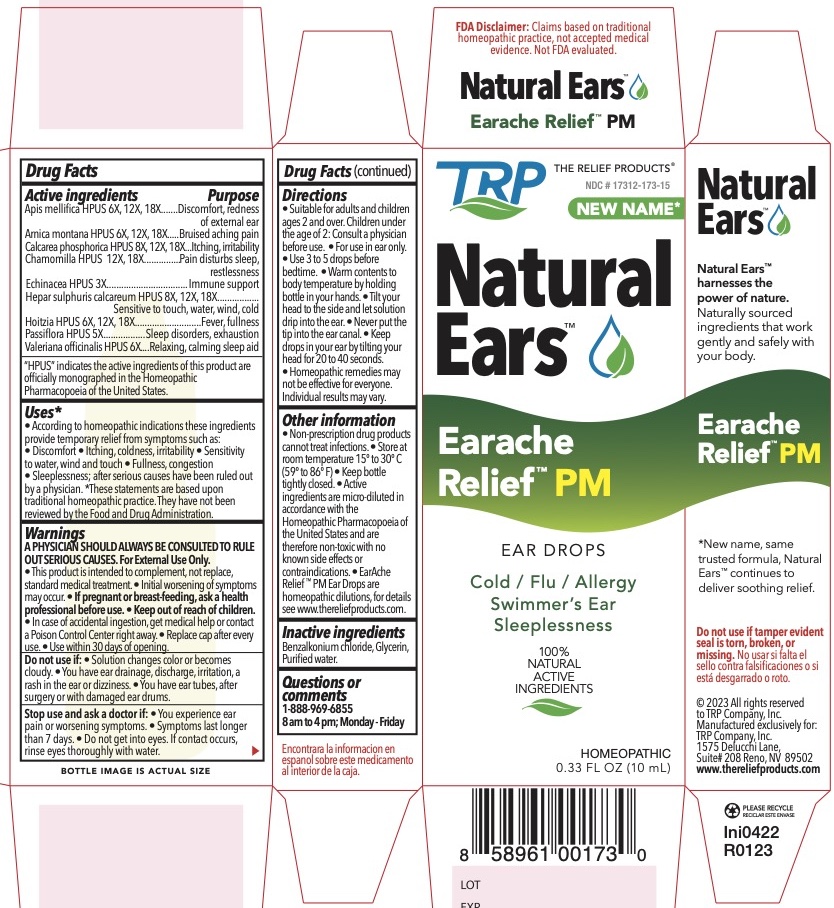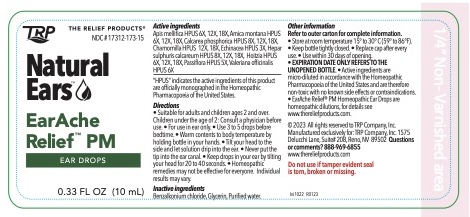 DRUG LABEL: EarAche Relief PM
NDC: 17312-173 | Form: LIQUID
Manufacturer: TRP Company
Category: homeopathic | Type: HUMAN OTC DRUG LABEL
Date: 20251215

ACTIVE INGREDIENTS: VALERIAN 6 [hp_X]/1 mL; ARNICA MONTANA 6 [hp_X]/1 mL; ECHINACEA ANGUSTIFOLIA 3 [hp_X]/1 mL; MATRICARIA CHAMOMILLA 12 [hp_X]/1 mL; APIS MELLIFERA 6 [hp_X]/1 mL; LOESELIA MEXICANA WHOLE 6 [hp_X]/1 mL; PASSIFLORA INCARNATA FLOWER 5 [hp_X]/1 mL; TRIBASIC CALCIUM PHOSPHATE 8 [hp_X]/1 mL; CALCIUM SULFIDE 8 [hp_X]/1 mL
INACTIVE INGREDIENTS: BENZALKONIUM CHLORIDE; GLYCERIN; WATER

EarAche Relief ® PM Nighttime Formula

ACTIVE INGREDIENT

Apis mellifica HPUS 6x, 12x, 18x...........................Discomfort, redness of external ear
Arnica montana HPUS 6x, 12x, 18x.......................Bruised aching pain
Calcarea phosphorica HPUS 8x, 12x, 18x.............Itching, irritability
Chamomilla HPUS 12x,18x....................................Pain disturbs sleep, restlessness
Echinacea HPUS 3x...............................................Immune support
Hepar sulphuris calcareum HPUS 8x, 12x, 18x......Sensitive to touch, water, wind, cold
Hoitzia HPUS 6x, 12x, 18x......................................Fever, fullness
Passiflora HPUS 5x ................................................Sleep disorders, exhaustion
Valeriana officinalis HPUS 6x..................................Relaxing, calming sleep aid

"HPUS" indicates the active ingredients are in the Homeopathic Pharmacopoeia of the United States.

PURPOSE

Apis mellifica HPUS - Discomfort, redness of external ear
Arnica montana HPUS - Bruised aching pain
Calcarea phosphorica HPUS - Itching, irritability
Chamomilla HPUS - Pain disturbs sleep, restlessness
Echinacea HPUS - Immune support
Hepar sulphuris calcareum - Sensitive to touch, water, wind, cold
Hoitzia HPUS - Fever, fullness
Passiflora HPUS - Sleep disorders, exhaustion
Valeriana officinalis HPUS - Relaxing, calming sleep aid

Uses:*
• According to homeopathic indications these ingredients provide temporary relief from symptoms such as: • Discomfort • Itching, coldness, irritability • Sensitivity to water, wind and touch • Fullness, congestion • Sleeplessness; after serious causes have been ruled out by a physician. *These statements are based upon traditional homeopathic practice. They have not been reviewed by the Food and Drug Administration.

*These statements are based upon traditional homeopathic practice. They have not been reviewed by the Food and Drug Administration.

Warnings:

A PHYSICIAN SHOULD ALWAYS BE CONSULTED TO RULE OUT SERIOUS CAUSES. For External Use Only.

- This product is intended to complement, not replace, standard medical treatment.
- Initial worsening of symptoms may occur.

Stop use and ask a doctor if: • You experience ear pain or worsening symptoms. • Symptoms last longer than 7 days.

PREGNANCY OR BREAST FEEDING

If pregnant or breast-feeding, ask a health professional before use.

Do not use:

- If solution changes color or becomes cloudy.
- If you have ear drainage, discharge, irritation, a rash in the ear or dizziness.
- If you have ear tubes, after surgery or with damaged ear drums.

Keep out of reach of children

WARNINGS

- In case of accidental ingestion, get medical help or contact a Poison Control Center right away.
- Do not get into eyes. If contact occurs, rinse eyes thoroughly with water.

Directions:
• Suitable for adults and children ages 2 and over. Children under the age of 2: Consult a physician before use. • For use in ear only.•Use 3 to 5 drops before bedtime. • Warm contents to body temperature by holding bottle in your hands. • Tilt your head to the side and let solution drip into the ear. • Never put the tip into the ear canal. • Keep drops in your ear by tilting your head for 20 to 40 seconds. • Homeopathic remedies may not be effective for everyone. Individual results may vary.

Other information:

• Non-prescription drug products cannot treat infections. • Store at room temperature 15o to 30o C (59o to 86o F) • Keep bottle tightly closed. • Active ingredients are micro-diluted in accordance with the Homeopathic Pharmacopoeia of the United States and are therefore non-toxic with no known side effects or contraindications. • EarAche Relief ® PM Ear Drops are homeopathic dilutions, for details see www.thereliefproducts.com.

Inactive Ingredients:
Benzalkonium Chloride, Glycerin, Purified Water.

Questions or comments?

www.thereliefproducts.com, 1-888-969-6855

PACKAGE LABEL

FDA Disclaimer: Claims based on traditional homeopathic practice, not accepted medical evidence. Not FDA evaluated.